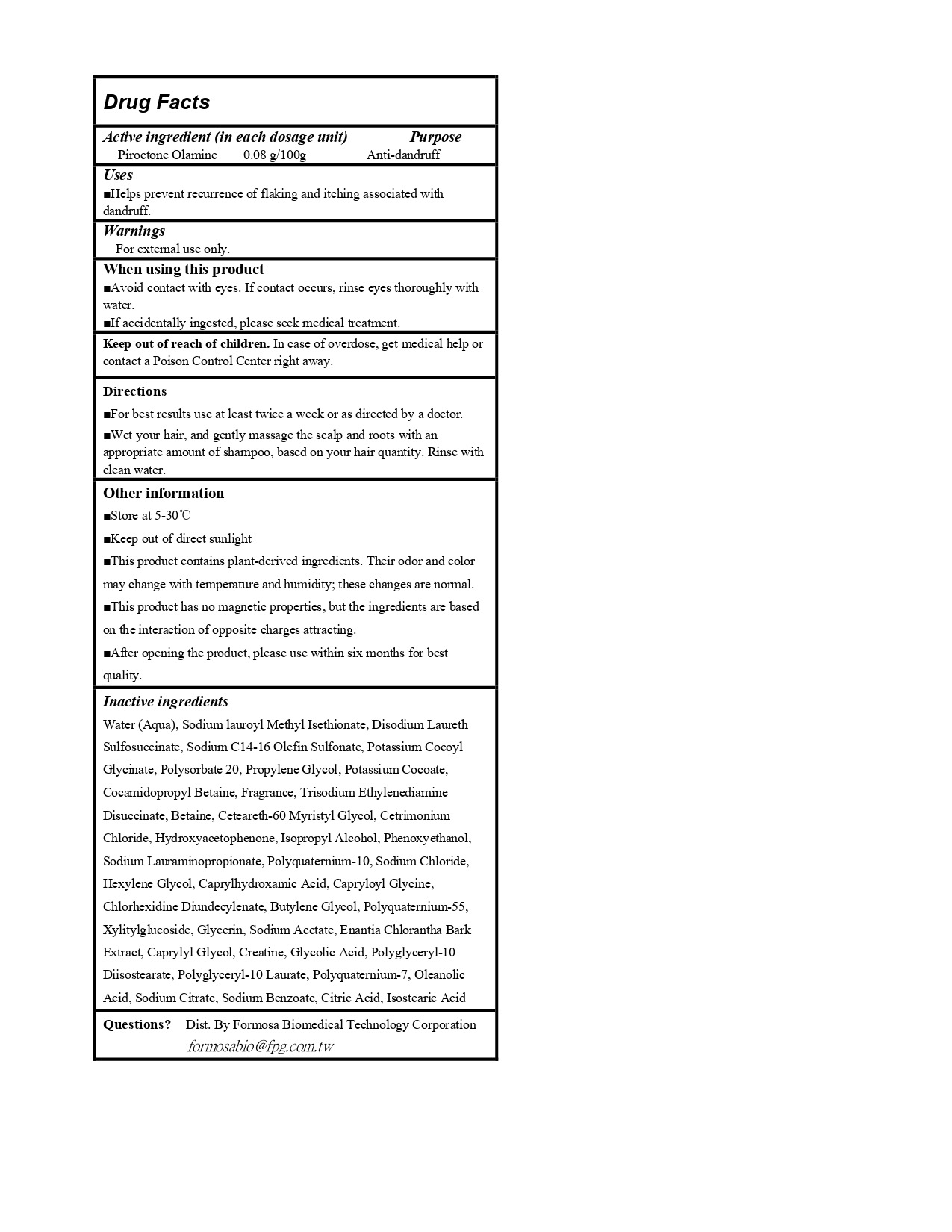 DRUG LABEL: FORTE Magnetic S3 Oil Control Anti-Dandfuff
NDC: 84655-101 | Form: LOTION/SHAMPOO
Manufacturer: FORMOSA BIOMEDICAL TECHNOLOGY CORPORATION
Category: otc | Type: HUMAN OTC DRUG LABEL
Date: 20240813

ACTIVE INGREDIENTS: PIROCTONE OLAMINE 0.4 g/500 g
INACTIVE INGREDIENTS: DISODIUM LAURETH SULFOSUCCINATE; ANNICKIA CHLORANTHA BARK; POTASSIUM COCOYL GLYCINATE; POTASSIUM COCOATE; TRISODIUM ETHYLENEDIAMINE DISUCCINATE; BUTYLENE GLYCOL; PROPYLENE GLYCOL; COCAMIDOPROPYL BETAINE; POLYGLYCERYL-10 LAURATE; SODIUM C14-16 OLEFIN SULFONATE; ISOSTEARIC ACID; POLYSORBATE 20; CREATINE; HEXYLENE GLYCOL; POLYQUATERNIUM-10 (400 CPS AT 2%); SODIUM LAUROYL METHYL ISETHIONATE; SODIUM CITRATE; POLYQUATERNIUM-55; OLEANOLIC ACID; SODIUM ACETATE; CAPRYLOYL GLYCINE; CETRIMONIUM CHLORIDE; PHENOXYETHANOL; WATER; BETAINE; POLYQUATERNIUM-7 (70/30 ACRYLAMIDE/DADMAC; 1600 KD); CAPRYLHYDROXAMIC ACID; ISOPROPYL ALCOHOL; CAPRYLYL GLYCOL; GLYCOLIC ACID; CITRIC ACID MONOHYDRATE; SODIUM CHLORIDE; FRAGRANCE 13576; XYLITYLGLUCOSIDE; GLYCERIN; CETEARETH-60 MYRISTYL GLYCOL; HYDROXYACETOPHENONE; SODIUM LAURAMINOPROPIONATE; SODIUM BENZOATE

Active ingredient: Piroctone Olamine 0.4g/500g

INDICATIONS AND USAGE

Uses: Helps prevent recurence of flaking and itching associated with dandruff

When using this product:
Avoid contact with eyes.If contact occurs,rinse eyes thoroughly with water.
If accidentally ingested,please seek medical treatment.

Keep out of reach of children.

In case of overdose,get medical help or contaet a Poison Control Center right away.

Directions:
For best results use at least twice a week or as directed by a doctor.
Wet your hair,and gently massage the scap and roots with an appropriate amount of shampoo,based on your hair quantity.Rinse with
clean water

Other information:
Store at 5-30C;
Keep out of direct sunlight;
This product contains plant-derived ingredients.Their odor and color may change with temperature and humidity; these changes are nomal;
This product has no magnetic properties, but the ingredients are based on the interaction of opposite charges attracting.

Inactive ingredients:

Water (Aqua), Sodium lauroyl Methyl Isethionate, Disodium Laureth Sulfosuccinate, Sodium C14-16 Olefin Sulfonate, Potassium Cocoyl Glycinate, Polysorbate 20, Propylene Glycol, Potassium Cocoate, Cocamidopropyl Betaine, Fragrance, Trisodium Ethylenediamine Disuccinate, Betaine, Ceteareth-60 Myristyl Glycol, Cetrimonium Chloride, Hydroxyacetophenone, Isopropyl Alcohol, Phenoxyethanol, Sodium Lauraminopropionate, Polyquaternium-10, Sodium Chloride, Hexylene Glycol, Caprylhydroxamic Acid, Capryloyl Glycine, Butylene Glycol, Polyquaternium-55, Xylitylglucoside, Glycerin, Sodium Acetate, Enantia Chlorantha Bark Extract, Caprylyl Glycol, Creatine, Glycolic Acid, Polyglyceryl-10 Laurate, Polyquaternium-7, Oleanolic Acid, Sodium Citrate, Sodium Benzoate, Citric Acid, Isostearic Acid

Questions?

Dist.By Formosa Biomedical Technology Corporation
formmosabio@fpg.com.tw